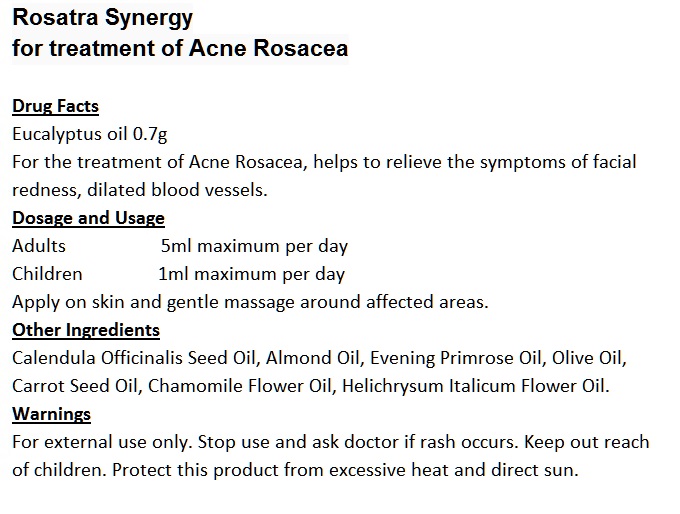 DRUG LABEL: Rosatra Synergy
NDC: 70470-1001 | Form: OIL
Manufacturer: PHYTOPIA CO., LTD.
Category: otc | Type: HUMAN OTC DRUG LABEL
Date: 20191231

ACTIVE INGREDIENTS: EUCALYPTOL 0.7 g/50 g
INACTIVE INGREDIENTS: HELICHRYSUM ITALICUM FLOWER OIL; TAMANU OIL; CALENDULA OFFICINALIS SEED OIL; ALMOND OIL; OLIVE OIL; CARROT SEED OIL; CHAMOMILE FLOWER OIL; EVENING PRIMROSE OIL

Warning

- For external use only.
- Stop use and ask doctor if rash occurs.
- Keep out reach of children.

Warning

Keep out reach of children.

Other Information

Protect this product from excessive heat and direct sun.

Drug Facts

Eucalyptol 0.7g

For the treatment of Acne Rosacea, helps to relieve the symptoms of facial redness, dilated blood vessels.

Dosage and Usage

Adults 5ml maximum per day

Children 1ml maximum per day

Apply on skin and gentle massage around affected areas.

INACTIVE INGREDIENT

Other Ingredients

Calendula Officinalis Seed Oil, Almond Oil, Evening Primrose Oil, Olive Oil, Carrot Seed Oil, Chamomile Flower Oil, Helichrysum Italicum Flower Oil.